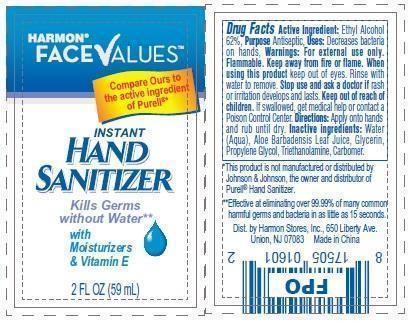 DRUG LABEL: Instant Hand Sanitizer
NDC: 63940-601 | Form: GEL
Manufacturer: Harmon Stores Inc
Category: otc | Type: HUMAN OTC DRUG LABEL
Date: 20171223

ACTIVE INGREDIENTS: ALCOHOL 620 mg/1 mL
INACTIVE INGREDIENTS: WATER; ALOE VERA LEAF; GLYCERIN; PROPYLENE GLYCOL; TROLAMINE

Instant Hand Sanitizer With Aloe

Active Ingredient

Ethyl Alcohol 62%

Purpose

Antiseptic

Uses

Decreases bacteria on hands

Warnings

For external use only

Flammable. Keep away from fire or flame

Stop use and ask a doctor

if rash or irritation develops and lasts

Keep out of reach of children

If swallowed, get medical help or contact a Poison Control Center.

Directions

Apply onto hands and rub until dry

Inactive Ingredients

Water, Aloe barbadensis Leaf Juice, Glycerin, Propylene Glycol, Triethanolamine, Carbomer